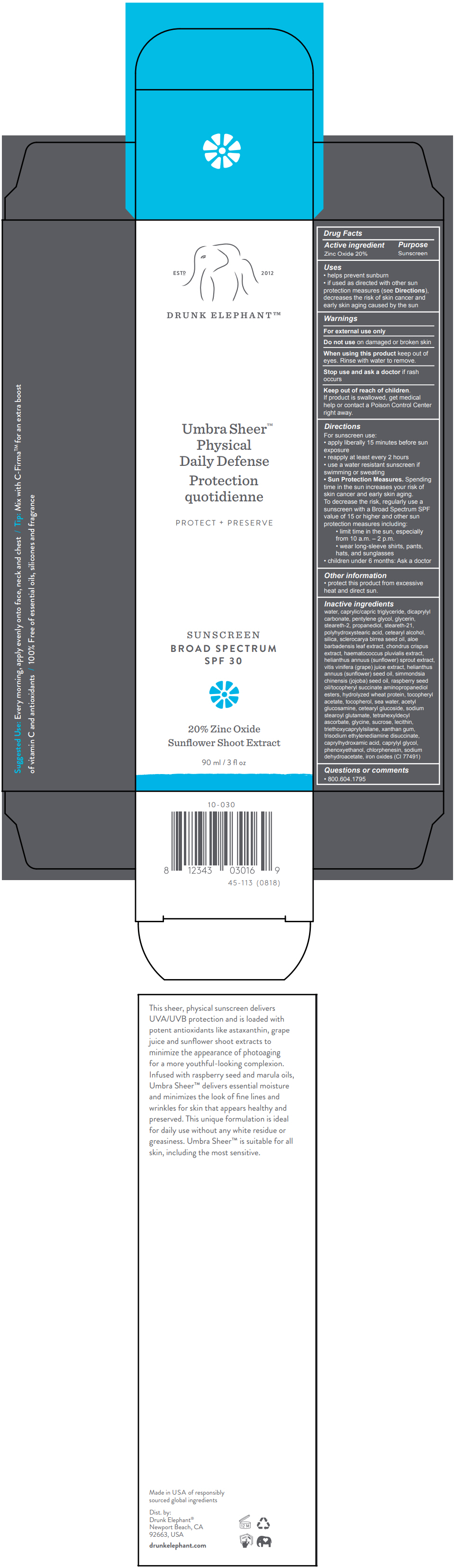 DRUG LABEL: Drunk Elephant 
NDC: 69455-964 | Form: LOTION
Manufacturer: Drunk Elephant, LLC
Category: otc | Type: HUMAN OTC DRUG LABEL
Date: 20220808

ACTIVE INGREDIENTS: ZINC OXIDE 20 mg/100 mL
INACTIVE INGREDIENTS: DICAPRYLYL CARBONATE; GLYCERIN; PENTYLENE GLYCOL; STEARETH-2; CETOSTEARYL ALCOHOL; STEARETH-21; SODIUM CHLORIDE; CHONDRUS CRISPUS; ALOE VERA LEAF; HELIANTHUS ANNUUS SPROUT; WINE GRAPE JUICE; WHEAT; SUNFLOWER OIL; JOJOBA OIL; SCLEROCARYA BIRREA SEED OIL; N-ACETYLGLUCOSAMINE; TETRAHEXYLDECYL ASCORBATE; RASPBERRY SEED OIL; .ALPHA.-TOCOPHEROL ACETATE; TOCOPHEROL; GLYCINE; SUCROSE; EGG PHOSPHOLIPIDS; SILICON DIOXIDE; POLYHYDROXYSTEARIC ACID (2300 MW); CAPRYLHYDROXAMIC ACID; EDETATE DISODIUM; TRIETHOXYCAPRYLYLSILANE; XANTHAN GUM; PROPANEDIOL; CAPRYLYL GLYCOL; PHENOXYETHANOL; WATER; .ALPHA.-TOCOPHEROL SUCCINATE, D-; HAEMATOCOCCUS PLUVIALIS; MEDIUM-CHAIN TRIGLYCERIDES; CETEARYL GLUCOSIDE; SODIUM STEAROYL GLUTAMATE; CHLORPHENESIN; SODIUM DEHYDROACETATE; FERRIC OXIDE RED

DRUNK ELEPHANT™ UMBRA SHEER™ DEFENSE
SPF-30

Drug Facts

Active ingredient

Zinc Oxide 20%

Purpose

Sunscreen

Uses

- helps prevent sunburn
- if used as directed with other sun protection measures (see Directions), decreases the risk of skin cancer and early skin aging caused by the sun

Warnings

For external use only

Do not use on damaged or broken skin

When using this product keep out of eyes. Rinse with water to remove.

Stop use and ask a doctor if rash occurs

Keep out of reach of children.

If product is swallowed, get medical help or contact a Poison Control Center right away.

Directions

For sunscreen use:

- apply liberally 15 minutes before sun exposure
- reapply at least every 2 hours
- use a water resistant sunscreen if swimming or sweating
- Sun Protection Measures. Spending time in the sun increases your risk of skin cancer and early skin aging.
  To decrease the risk, regularly use a sunscreen with a Broad Spectrum SPF value of 15 or higher and other sun protection measures including:
  - limit time in the sun, especially from 10 a.m. – 2 p.m.
  - wear long-sleeve shirts, pants, hats, and sunglasses
- children under 6 months: Ask a doctor

Other information

- protect this product from excessive heat and direct sun.

Inactive ingredients

water, caprylic/capric triglyceride, dicaprylyl carbonate, pentylene glycol, glycerin, steareth-2, propanediol, steareth-21, polyhydroxystearic acid, cetearyl alcohol, silica, sclerocarya birrea seed oil, aloe barbadensis leaf extract, chondrus crispus extract, haematococcus pluvialis extract, helianthus annuus (sunflower) sprout extract, vitis vinifera (grape) juice extract, helianthus annuus (sunflower) seed oil, simmondsia chinensis (jojoba) seed oil, raspberry seed oil/tocopheryl succinate aminopropanediol esters, hydrolyzed wheat protein, tocopheryl acetate, tocopherol, sea water, acetyl glucosamine, cetearyl glucoside, sodium stearoyl glutamate, tetrahexyldecyl ascorbate, glycine, sucrose, lecithin, triethoxycaprylylsilane, xanthan gum, trisodium ethylenediamine disuccinate, caprylhydroxamic acid, caprylyl glycol, phenoxyethanol, chlorphenesin, sodium dehydroacetate, iron oxides (CI 77491)

Questions or comments

- 800.604.1795

Dist. by:
Drunk Elephant®
Newport Beach, CA
92663, USA

PRINCIPAL DISPLAY PANEL - 90 ml Tube Box

ESTD
2012

DRUNK ELEPHANT™

Umbra Sheer™
Physical
Daily Defense

PROTECT + PRESERVE

SUNSCREEN
BROAD SPECTRUM
SPF 30

20% Zinc Oxide
Sunflower Shoot Extract

90 ml / 3 fl oz